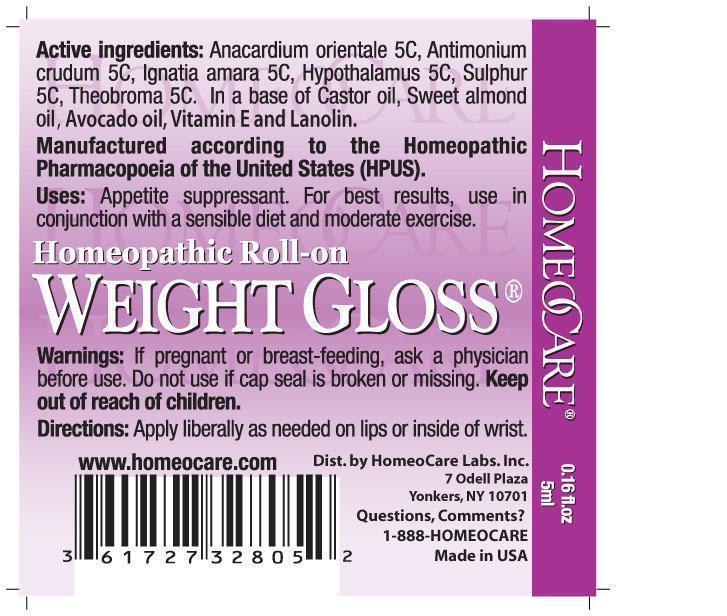 DRUG LABEL: Weight Gloss
NDC: 61727-328 | Form: LIPSTICK
Manufacturer: Homeocare Laboratories
Category: homeopathic | Type: HUMAN OTC DRUG LABEL
Date: 20181231

ACTIVE INGREDIENTS: SEMECARPUS ANACARDIUM JUICE 5 [hp_C]/5 mL; ANTIMONY TRISULFIDE 5 [hp_C]/5 mL; STRYCHNOS IGNATII SEED 5 [hp_C]/5 mL; BOS TAURUS HYPOTHALAMUS 5 [hp_C]/5 mL; SULFUR 5 [hp_C]/5 mL; COCOA 5 [hp_C]/5 mL
INACTIVE INGREDIENTS: CASTOR OIL; ALMOND OIL; AVOCADO OIL; .ALPHA.-TOCOPHEROL; LANOLIN

Weight Gloss

Active ingredients:

Anacardium orientale 5C, Antimonium crudum 5C, Ignatia amara 5C, Hypothalamus 5C, Sulphur 5C, Theobroma 5C.

Inactive ingredients:

In a base of Castor oil, Sweet almond oil, Avocado oil, Vitamin E and Lanolin.

Purpose:

Appetite suppressant. For best results, use in conjunction with a sensible diet and moderate exercise.

Warnings:

If pregnant or breast-feeding, ask a physician before use. Do not use if cap seal is broken or missing. Keep out of reach of children.

Keep out of reach of children.

Indications and Usage:

Apply liberally as needed on lips or inside of wrist.

Dosage and Administration:

Apply liberally as needed on lips or inside of wrist.

Weight Gloss

Homeopathic Roll-on

weight gloss 2012.jpg